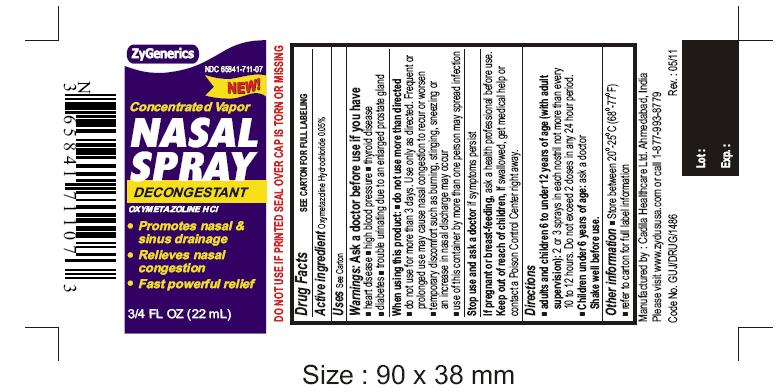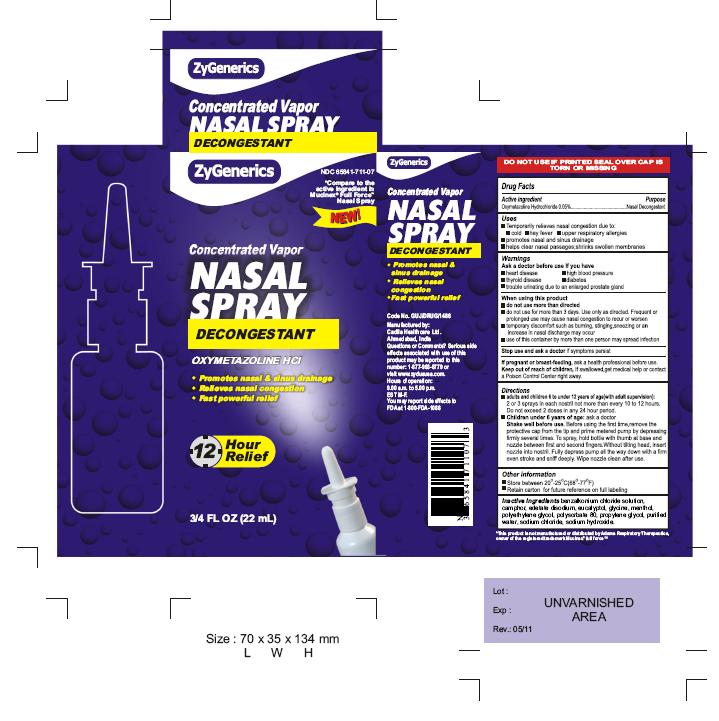 DRUG LABEL: OXYMETAZOLINE HYDROCHLORIDE
NDC: 65841-711 | Form: SPRAY, METERED
Manufacturer: Cadila Healthcare Limited
Category: otc | Type: HUMAN OTC DRUG LABEL
Date: 20110531

ACTIVE INGREDIENTS: OXYMETAZOLINE HYDROCHLORIDE 0.5 mg/1 mL
INACTIVE INGREDIENTS: EDETATE DISODIUM; EUCALYPTOL; GLYCINE; POLYETHYLENE GLYCOL; POLYSORBATE 80; PROPYLENE GLYCOL; SODIUM CHLORIDE; SODIUM HYDROXIDE; WATER; BENZALKONIUM CHLORIDE; MENTHOL; CAMPHOR (NATURAL)

Oxymetazoline Hydrochloride Concentrated Vapor Nasal Spray, 3/4 FL OZ (22 mL)

ACTIVE INGREDIENT

Oxymetazoline hydrochloride 0.05%

PURPOSE

Nasal decongestant

USES

- Temporarily relieves nasal congestion due to:

■ a cold ■ hay fever ■ upper respiratory allergies

- promotes nasal and sinus drainage
- temporarily relieves sinus congestion and pressure
- helps clear nasal passages; shrinks swollen membranes

WARNINGS

Ask a doctor before use if you have

■ heart disease ■ high blood pressure ■ thyroid disease ■ diabetes

■ trouble urinating due to an enlarged prostate gland

When using this product

- do not use more than directed
- do not use for more than 3 days. Use only as directed. Frequent or prolonged use may cause nasal congestion to recur or worsen.
- temporary discomfort such as burning, stinging, sneezing or an increase in nasal discharge may occur
- use of this container by more than one person may spread infection

Stop use and ask a doctor if symptoms persist.

If pregnant or breast-feeding, ask a health professional before use.

Keep out of reach of children

If swallowed, get medical help or contact a Poison Control Center right away.

Directions

- adults and children 6 to under 12 years of age (with adult supervision):

2 or 3 sprays in each nostril not more than every 10 to 12 hours. Do not exceed 2 doses in any 24-hour period.

- children under 6 years of age: ask a doctor.

Shake well before use. Before using the first time, remove the protective cap from the tip and prime metered pump by depressing firmly several times. To spray, hold bottle with thumb at base and nozzle between first and second fingers. Without tilting head, insert nozzle into nostril. Fully depress pump all the way down with a firm even stroke and sniff deeply. Wipe nozzle clean after use.

Other information

- Store between 20º - 25ºC (68º - 77ºF)
- retain carton for future reference on full labeling

Inactive ingredients

benzalkonium chloride solution, camphor, edetate disodium, eucalyptol, glycin, menthol, polyethylene glycol, polysorbate 80, propylene glycol, purified water, sodium chloride, sodium hydroxide.

Manufactured by:

Cadila Healthcare Ltd.

Ahmedabad, India

Rev.: 00/00

Revision Date: 05/31/2011

Container and Carton Labels

NDC 65841-711-07

Oxymetazoline Hydrochloride Concentrated Vapor Nasal Spray, ¾ FL OZ (22 mL)

Rx only

Zydus